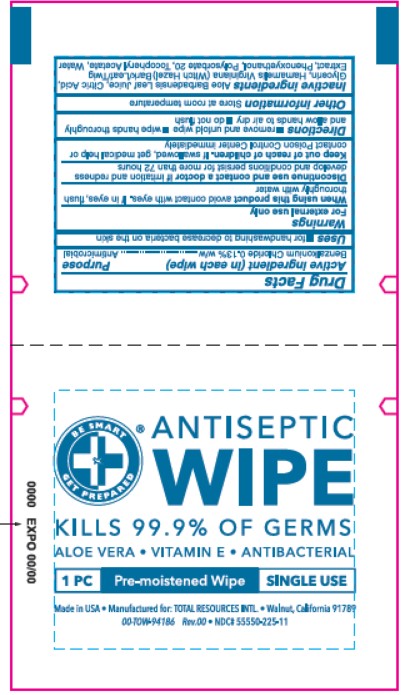 DRUG LABEL: ANTISEPTIC WIPE
NDC: 55550-225 | Form: CLOTH
Manufacturer: Total Resources International
Category: otc | Type: HUMAN OTC DRUG LABEL
Date: 20231218

ACTIVE INGREDIENTS: BENZALKONIUM CHLORIDE 13 g/100 g
INACTIVE INGREDIENTS: GLYCERIN; WATER; POLYSORBATE 20; HAMAMELIS VIRGINIANA LEAF; ALOE VERA LEAF; .ALPHA.-TOCOPHEROL ACETATE; ANHYDROUS CITRIC ACID; PHENOXYETHANOL

Total Resources International
ANTISEPTIC WIPE

Active Ingredient

Benzalkonium Chloride 0.13% w/w

Purpose

Antimicrobial

Uses

for handwashing to decrease bacteria on the skin

Warnings

For external use only

When using this product avoid contact with eyes. If in eyes flush thoroughly with water

Discontinue use and contact a doctor if irritation and redness develop and conditions persist for more than 72 hours

Keep out of reach of children

Keeo out of reach of children. If swallowed, get medical help or contact Poison Control Center immediately.

Directions

- remove and unfold wipe
- wipe hands thoroughly and allow hands to air dry
- do not flush

Other information

Store at room temperature

Inactive ingredients

Aloe Barbadensis Leaf Juice, Citric Acid, Glycerin, Hamamelis Virginiana (Witch Hazel) Bark/Leaf/Twig Extract, Phenoxyethanol, Polysorbate 20, Tocopheryl Acetate, Water

Label

ANTISEPTIC WIPE

BE SMART GET PREPARED

KILLS 99.9% OF GERMS

- ALOE VERA
- VITAMIN E
- ANTIBACTERIAL

1 PC, Pre- moistened Wipe, SINGLE USE

- Made in USA
- Manufactured for: TOTAL RESOURCES INTL.
- Walnut, California 91789
- 00-TOW-94186 Rev.00
- NDC# 55550-225-11